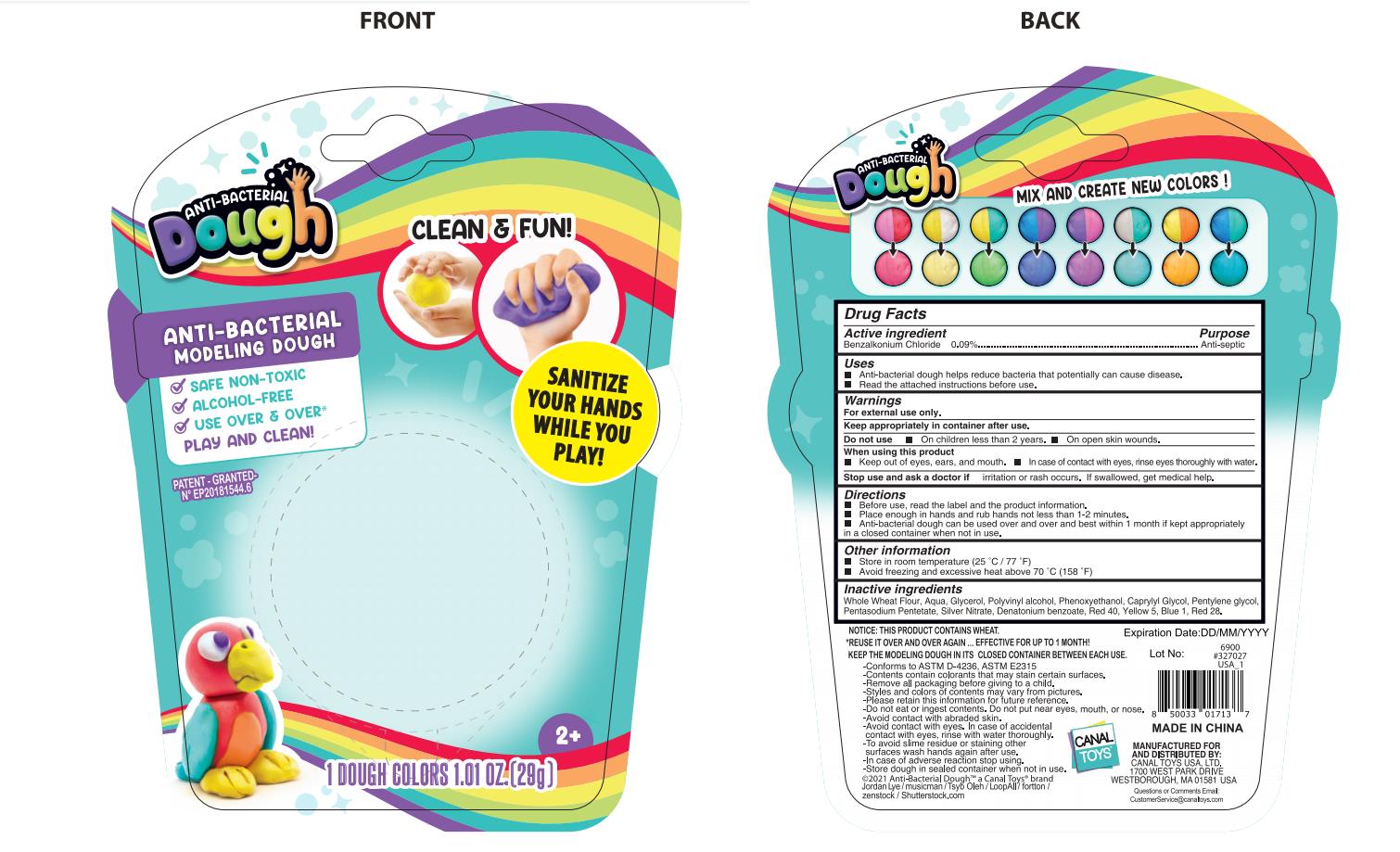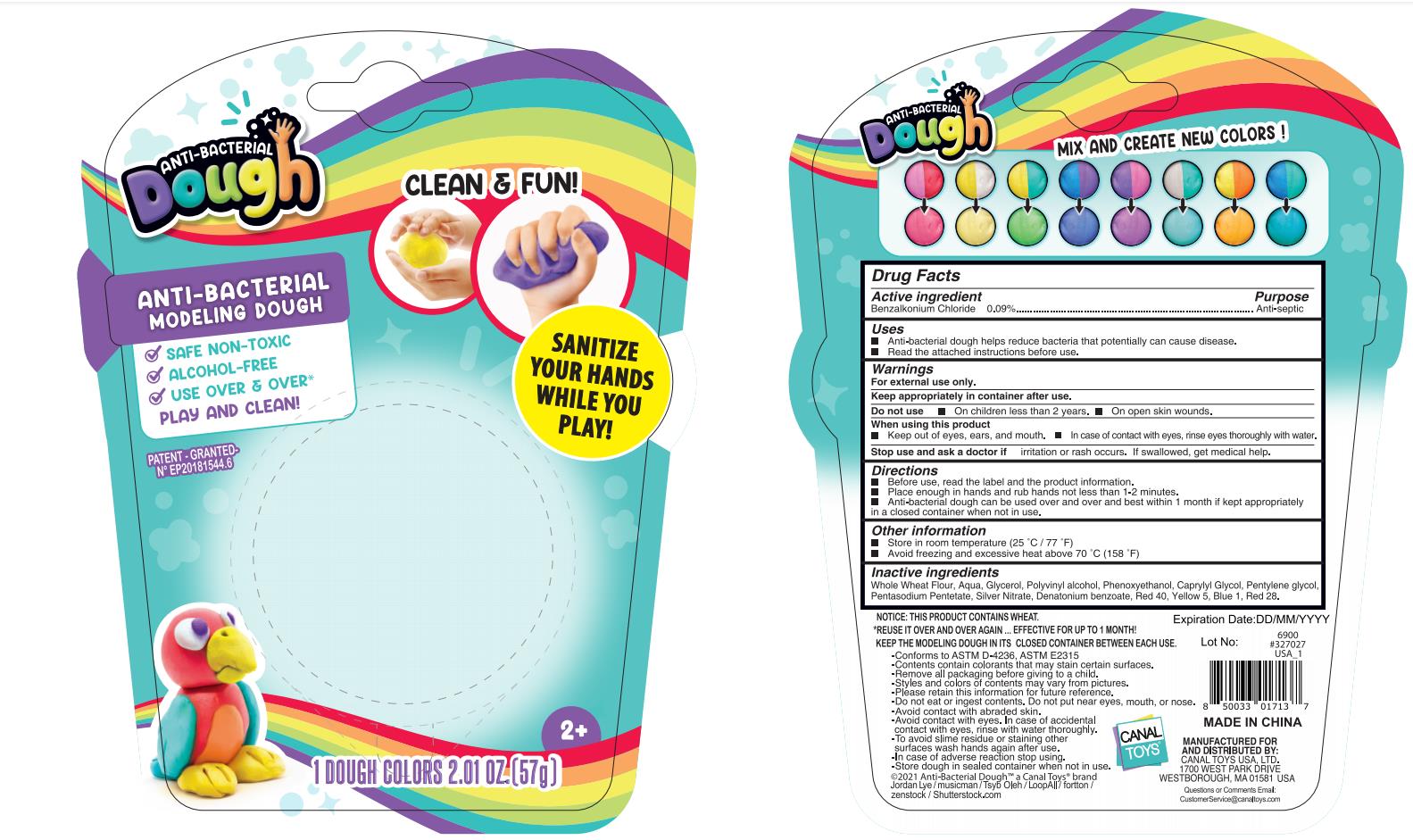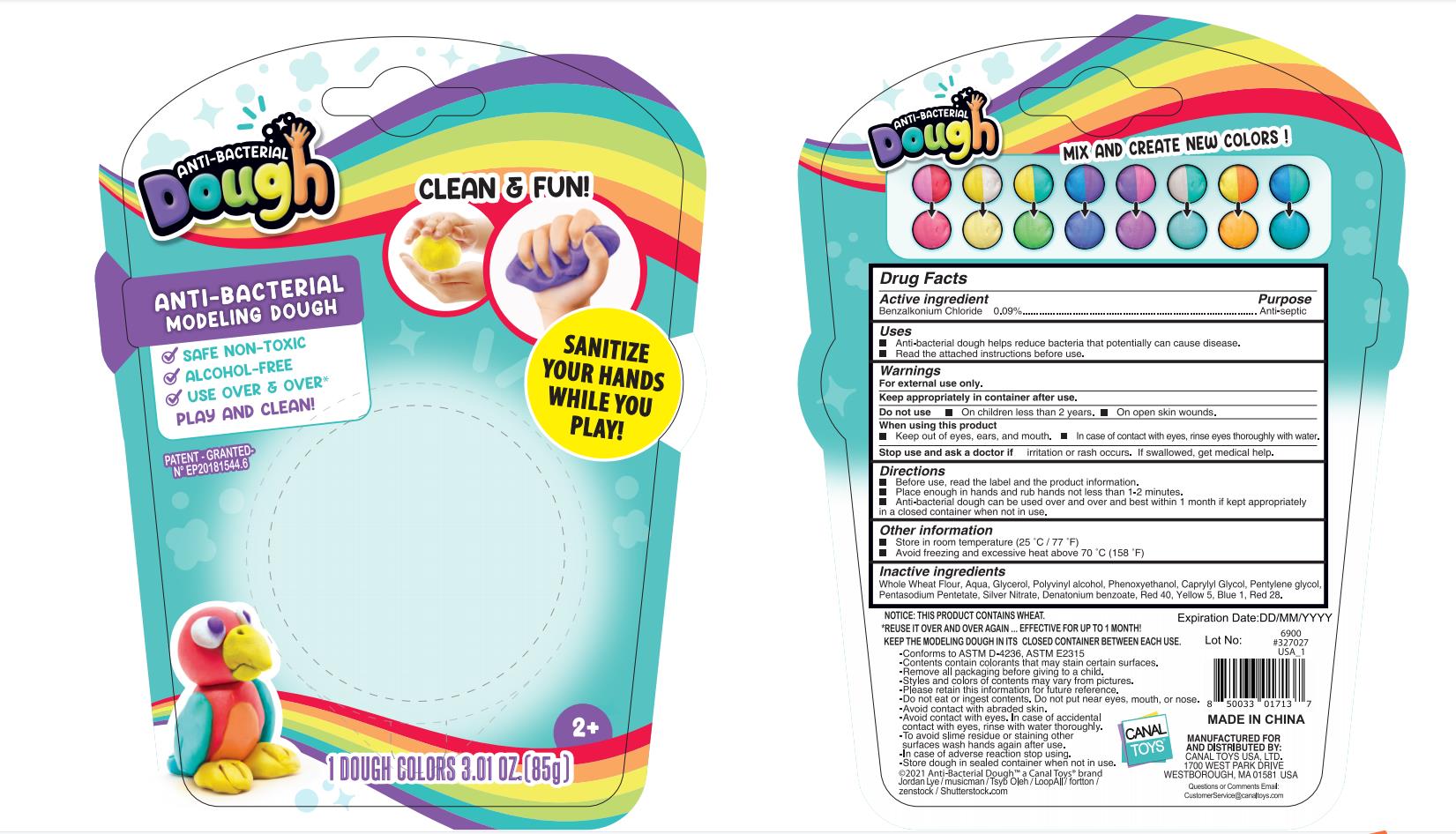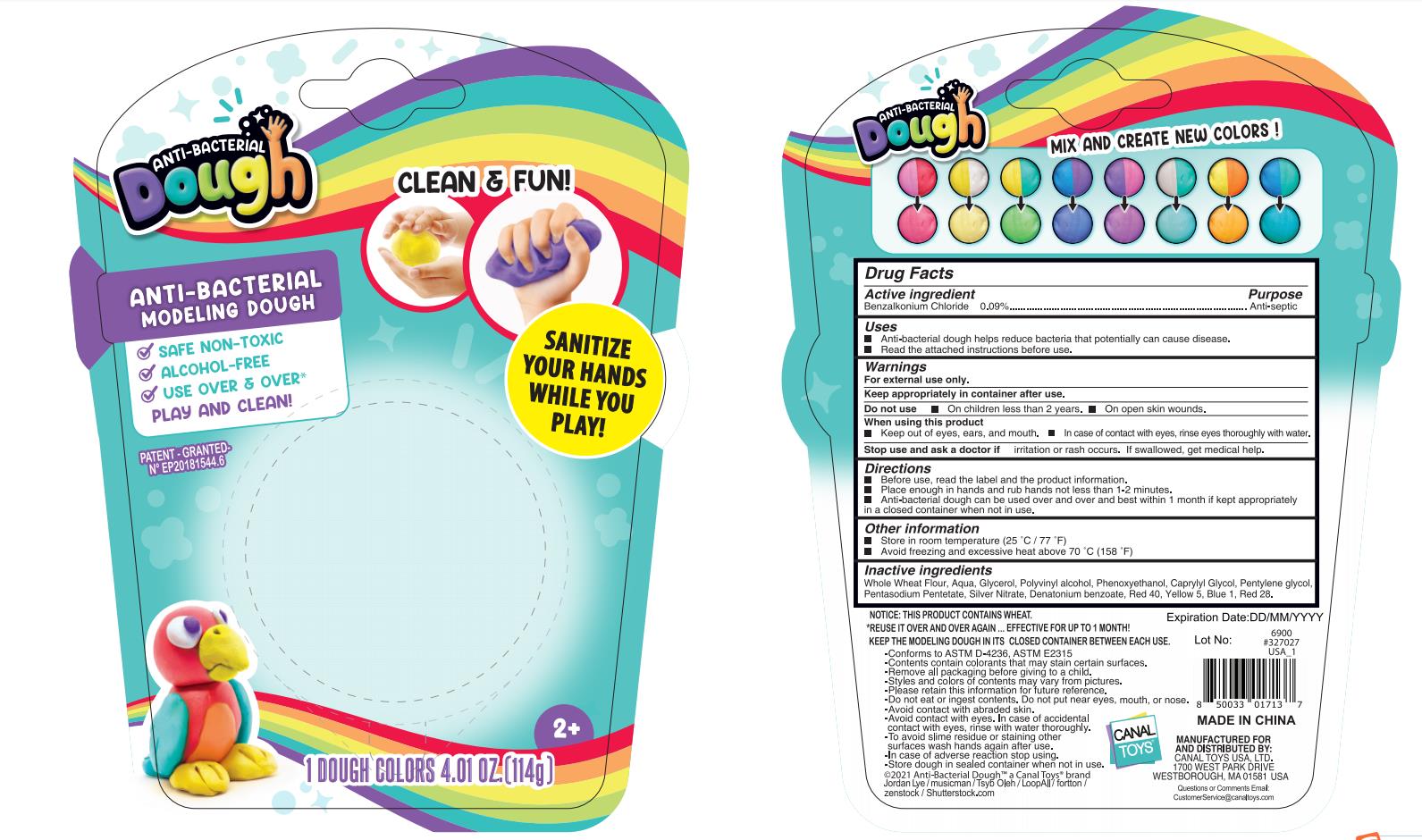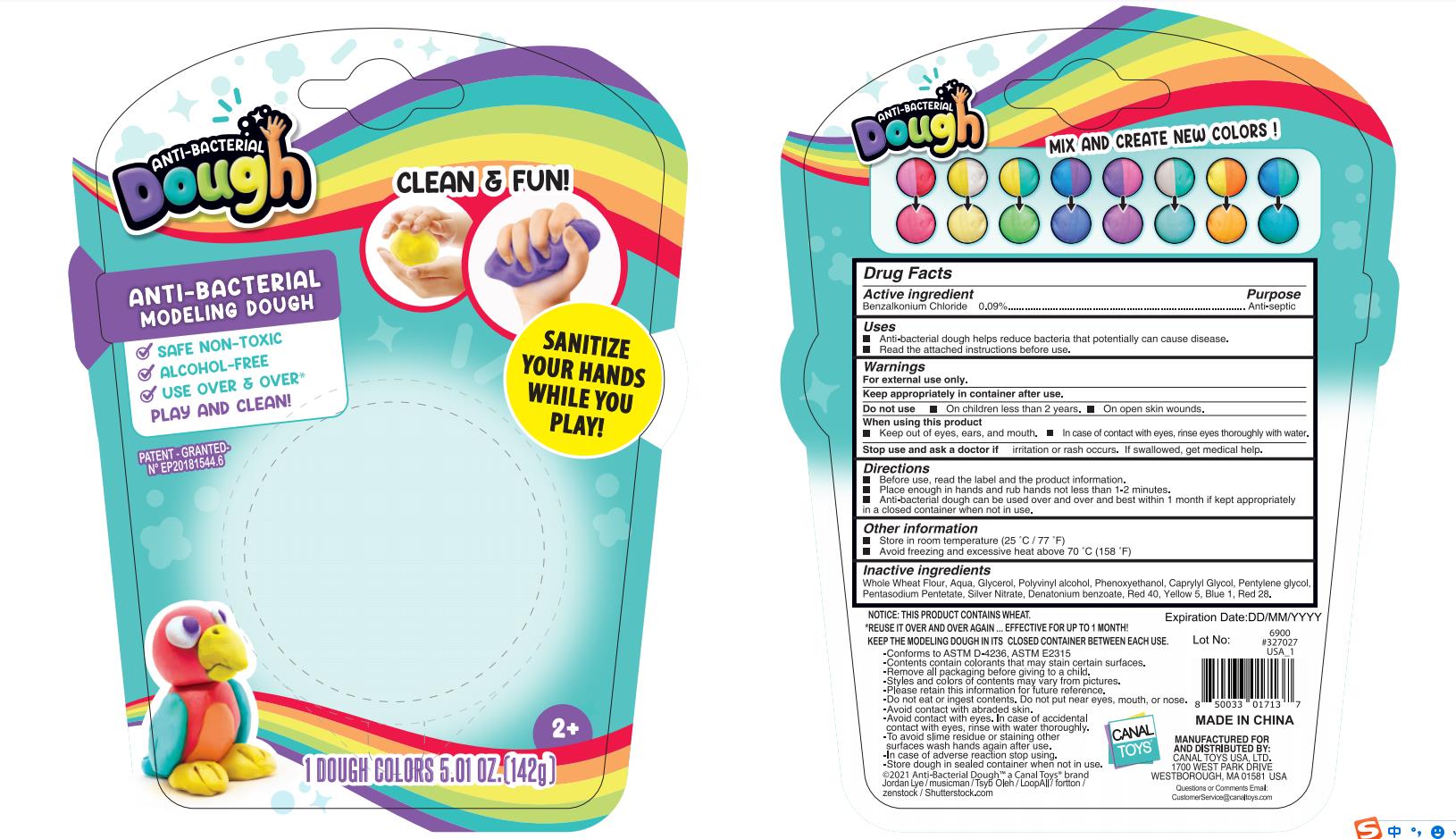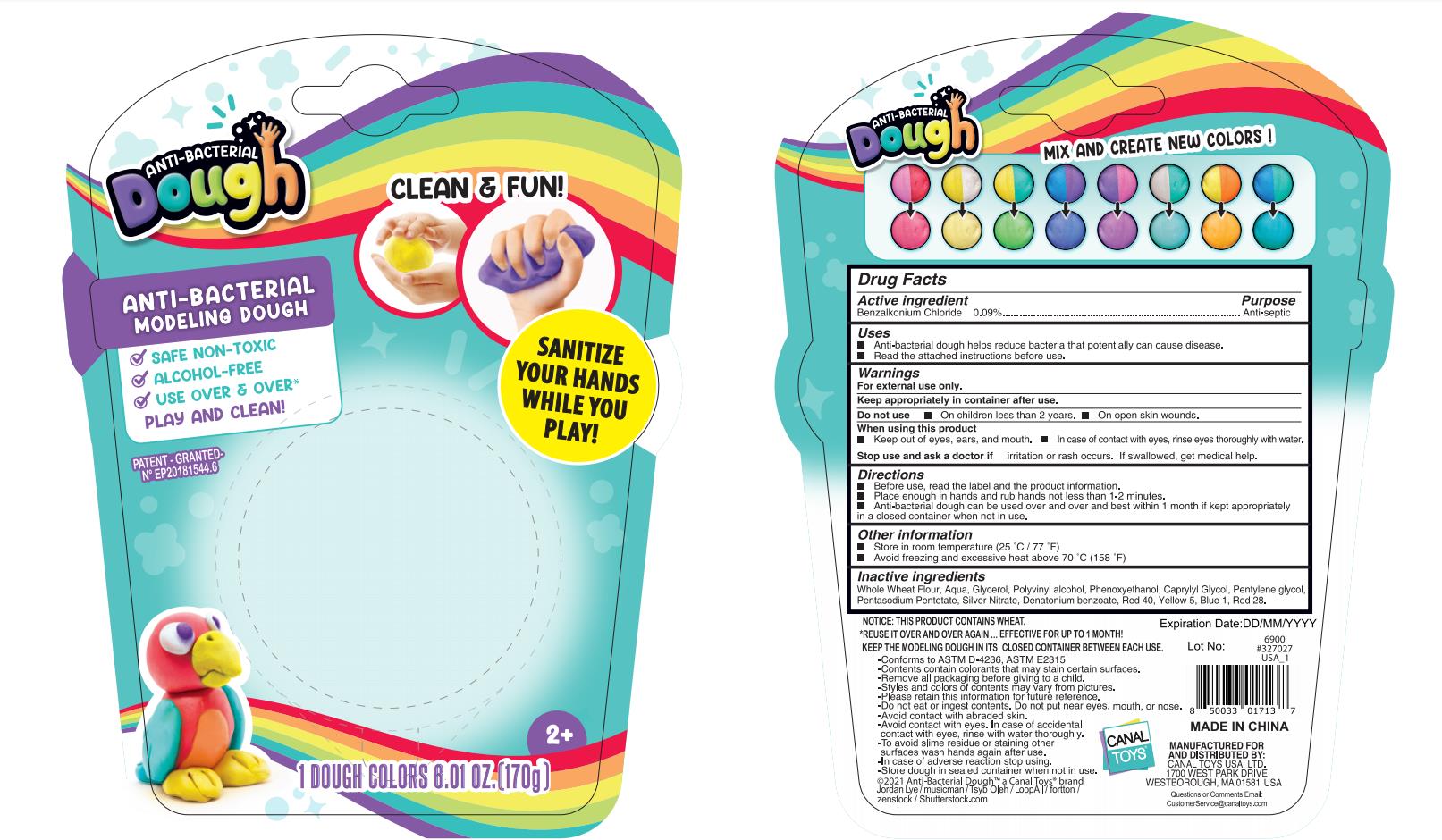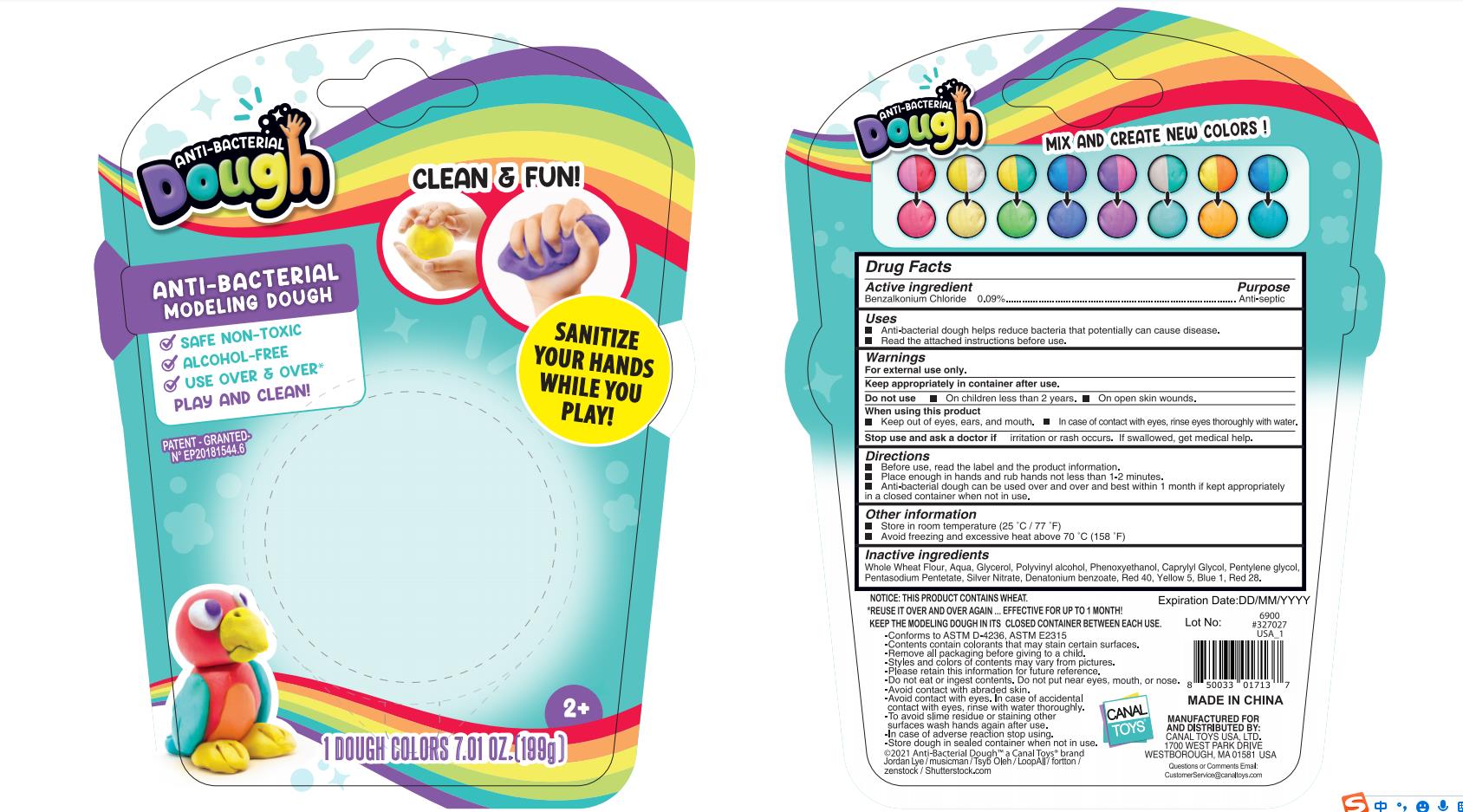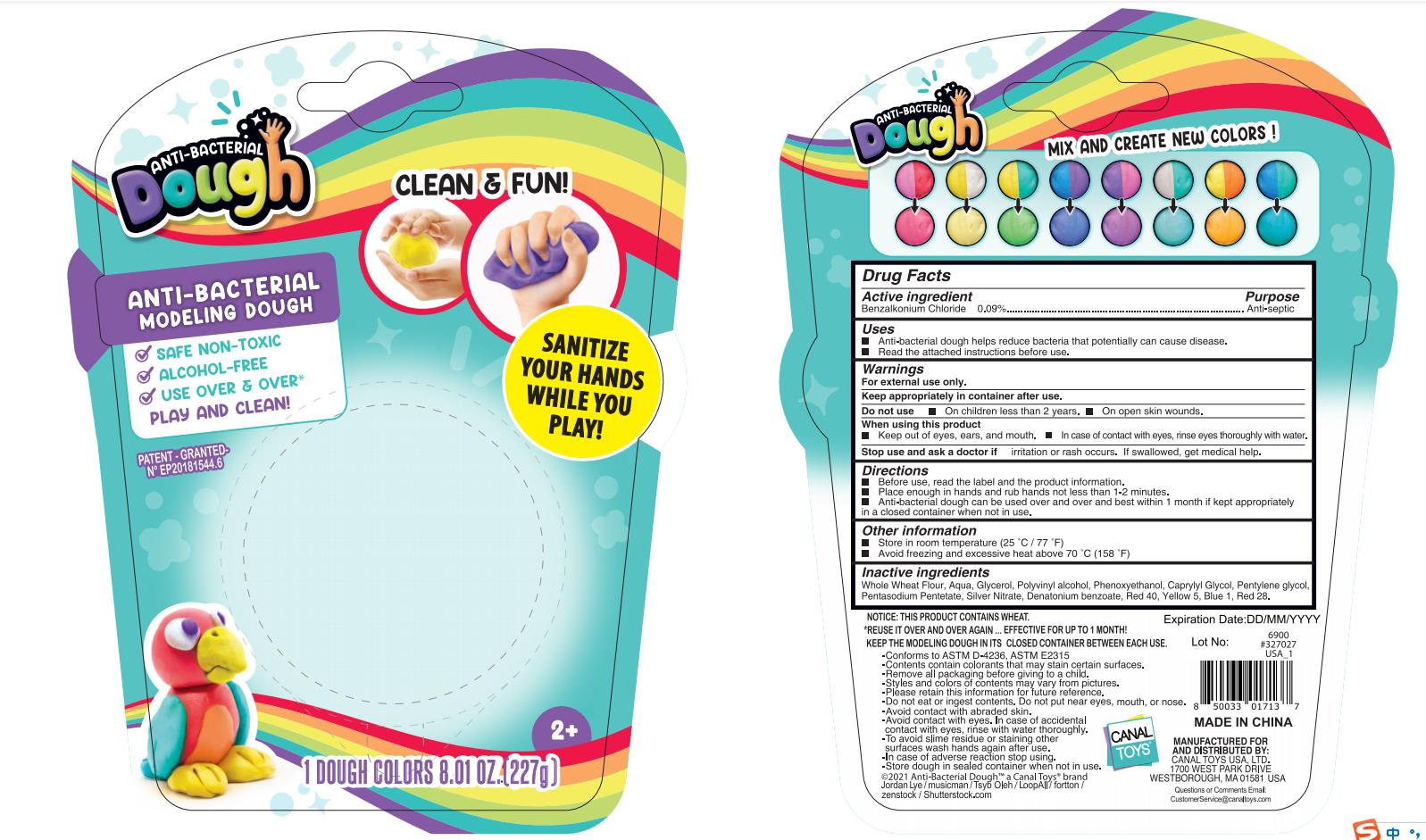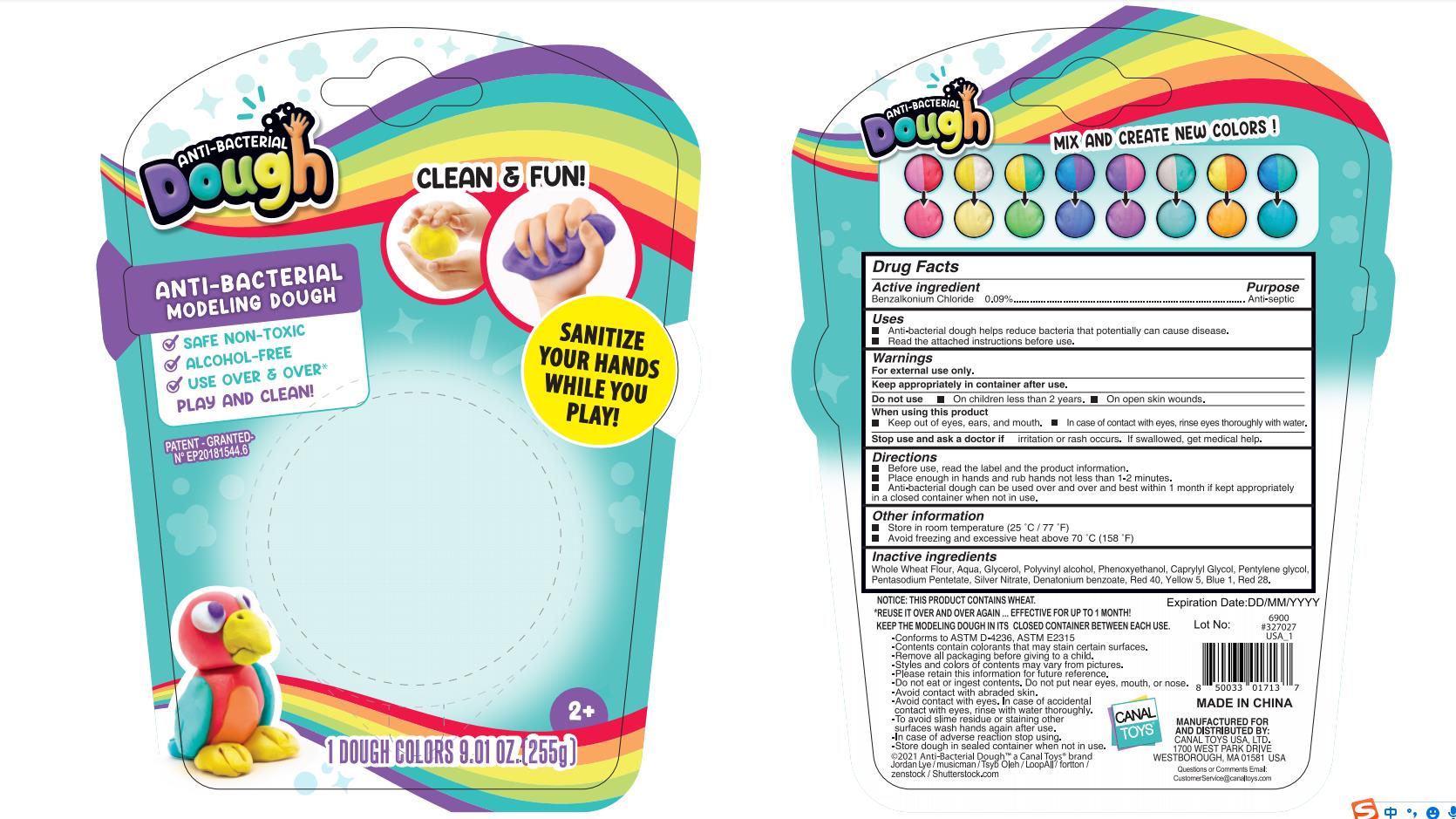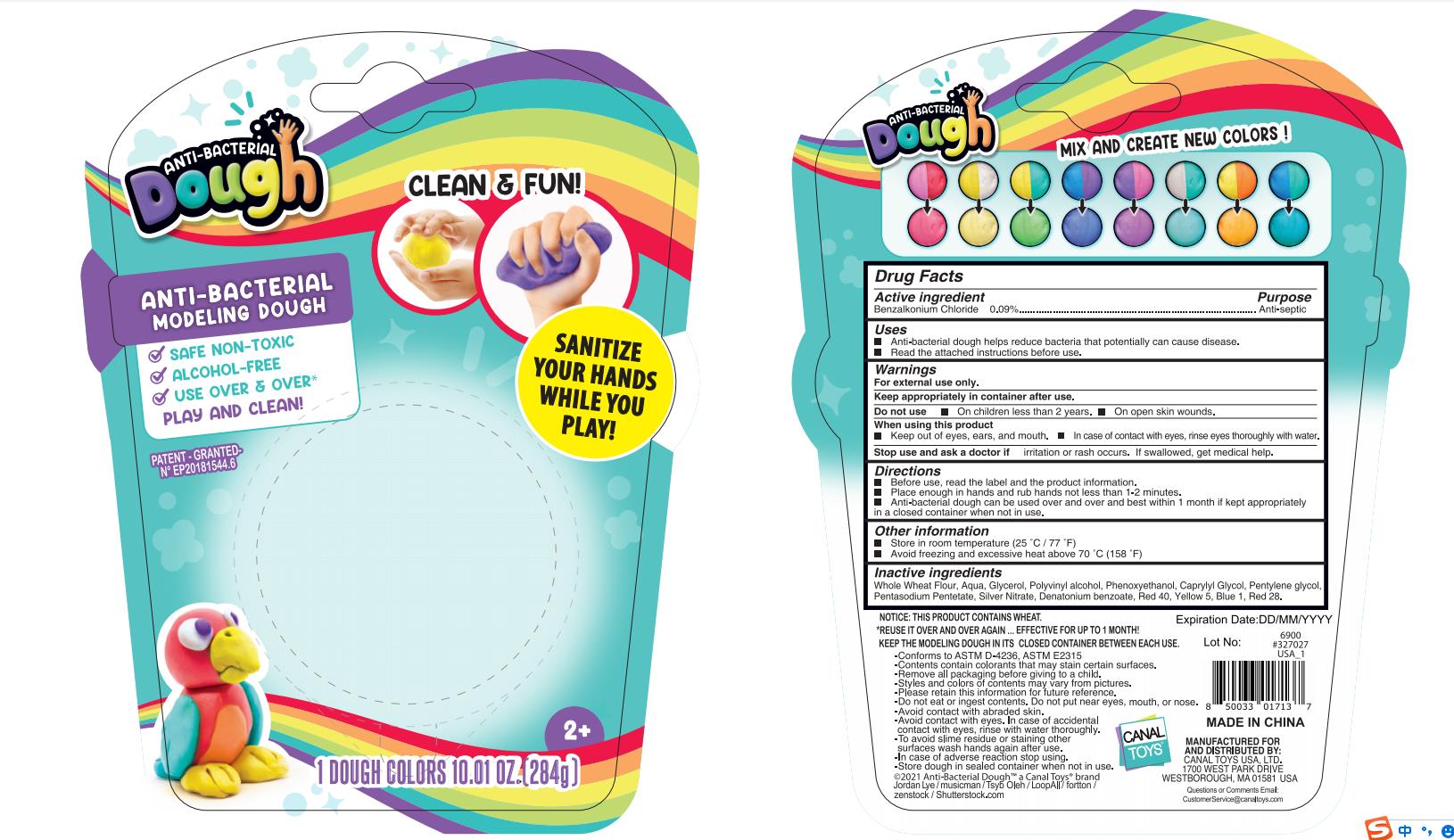 DRUG LABEL: ANTI-BACTERIAL DOUGH
NDC: 78048-016 | Form: GEL
Manufacturer: Dongguan City Dexu Toys Co., Ltd.
Category: otc | Type: HUMAN OTC DRUG LABEL
Date: 20211223

ACTIVE INGREDIENTS: BENZALKONIUM CHLORIDE 0.09 g/100 g
INACTIVE INGREDIENTS: FD&C RED NO. 40; PENTYLENE GLYCOL; CAPRYLYL GLYCOL; GLYCERIN; WHEAT; WATER; POLYVINYL ALCOHOL, UNSPECIFIED; SILVER NITRATE; PHENOXYETHANOL; FD&C BLUE NO. 1; PENTASODIUM PENTETATE; D&C RED NO. 28; DENATONIUM BENZOATE; FD&C YELLOW NO. 5

78048-016
ANTI-BACTERIAL DOUGH

Active Ingredient(s)

Benzalkonium Chloride 0.09%

Purpose

Anti-septic

Use

Anti-bacterial dough helps reduce bacteria that potentially can cause disease.

Read the attached instructions before use.

Warnings

For external use only.
Keep appropriately in container after use.

Do not use

in children less than 3.
on open skin wounds.

When using this product

Keep out of eyes, ears, and mouth.
in case of contact with eyes, rinse eyes thoroughly with water.

Stop use

Stop use and ask a doctor if irritation or rash occurs.
If swallowed, get medical help.

Keep out of eyes , ears , and mouth.

In case of contact with eyes , rinse eyes thoroughly with water.

Directions

Before use,read the label and the product information.

Place enough in hands and rub hands not less than 1-2 minutes.

Anti-bacterial dough can be used over and over and best within 1 month if kept appropriatelya closed container when not in use.

Other information

Store in room temperature (25℃ / 77 ℉)

Avoid freezing and excessive heat above 70 ℃ (158 ℉)

Inactive ingredients

Whole Wheat Flour , Aqua , Glycerol , Polyvinyl alcohol , Phenoxyethanol , Caprylyl Glycol , Pentylene glycol, Pentasodium Pentetate, Silver Nitrate, Denatonium benzoate, Red 40,Yellow 5, Blue 1, Red 28